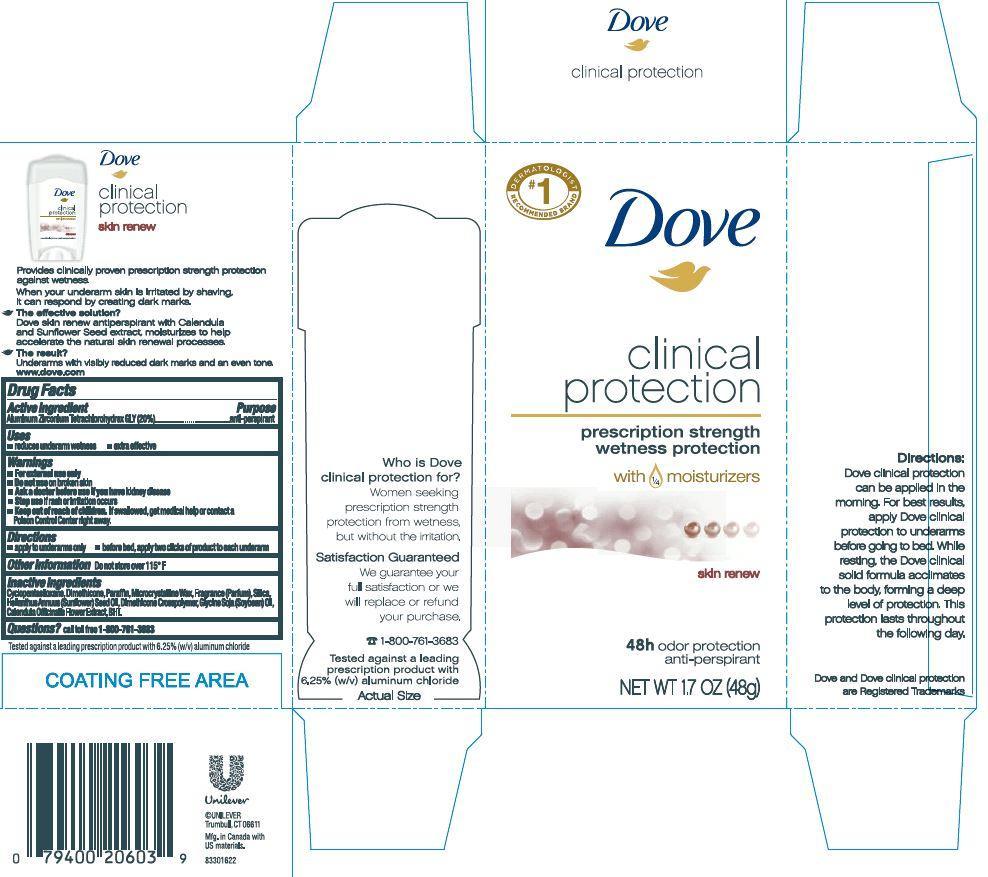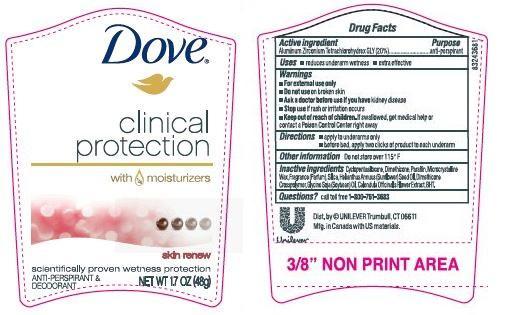 DRUG LABEL: Dove
NDC: 64942-1439 | Form: STICK
Manufacturer: Conopco Inc. d/b/a Unilever
Category: otc | Type: HUMAN OTC DRUG LABEL
Date: 20241024

ACTIVE INGREDIENTS: ALUMINUM ZIRCONIUM TETRACHLOROHYDREX GLY 20 g/100 g
INACTIVE INGREDIENTS: CYCLOMETHICONE 5; DIMETHICONE; MICROCRYSTALLINE WAX; SILICON DIOXIDE; SUNFLOWER OIL; PARAFFIN; CALENDULA OFFICINALIS FLOWER; SOYBEAN OIL; BUTYLATED HYDROXYTOLUENE

Dove Clinical Protection Skin Renew Antiperspirant

Active Ingredient

Aluminum Zirconium Tetrachlorohydrex GLY (20%)

Purpose
anti-perspirant

Uses
• reduces underarm wetness
• extra effective

Warnings
• For external use only

• Do not use on broken skin

• Ask a doctor before use if you have kidney disease

• Stop use if rash or irritation occurs

• Keep out of reach of children. If swallowed, get medical help or contact a Poison Control Center right away.

Directions
• apply to underarms only
• before bed, apply two clicks of product to each underarm

Inactive ingredients
Cyclopentasiloxane, Dimethicone, Paraffin, Microcrystalline Wax, Fragrance (Parfum), Silica, Helianthus Annuus (Sunflower) Seed Oil, Dimethicone Crosspolymer, Glycine Soja (Soybean) Oil, Calendula Officinalis Flower Extract, BHT.

Questions? Call toll-free 1-800-761-3683